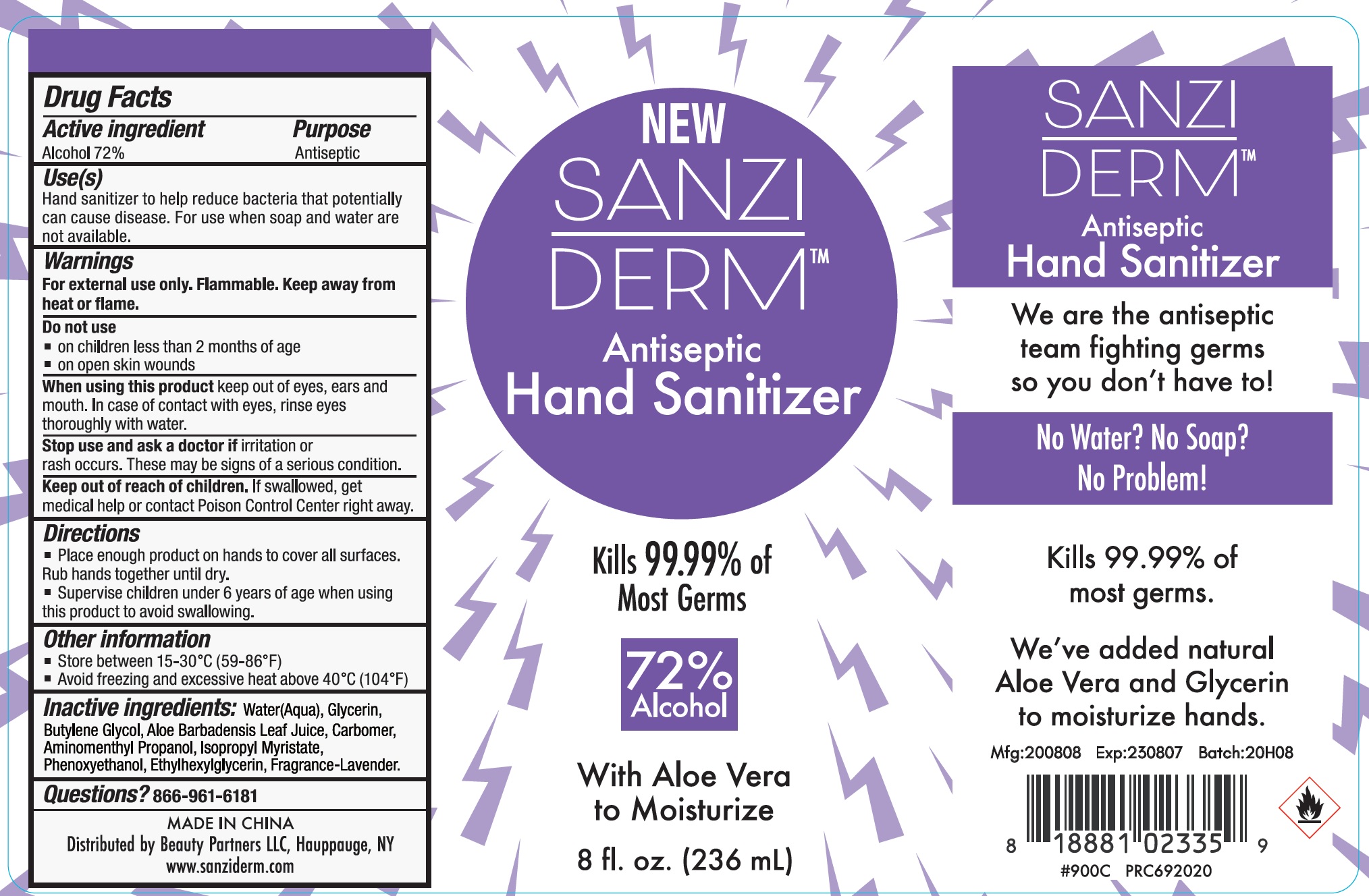 DRUG LABEL: Antiseptic Hand Sanitizer
NDC: 78229-005 | Form: GEL
Manufacturer: Beauty Partners LLC
Category: otc | Type: HUMAN OTC DRUG LABEL
Date: 20231108

ACTIVE INGREDIENTS: ALCOHOL 0.72 mL/1 mL
INACTIVE INGREDIENTS: WATER; GLYCERIN; BUTYL GLYCOLATE; ALOE VERA LEAF; CARBOMER HOMOPOLYMER, UNSPECIFIED TYPE; AMINOMETHYLPROPANOL; ISOPROPYL MYRISTATE; PHENOXYETHANOL; ETHYLHEXYLGLYCERIN

Antiseptic Hand Sanitizer

Active ingredient

Alcohol 72%

Purpose

Antiseptic

Use(s)

Hand sanitizer to help reduce bacteria that potentially can cause disease. For use when soap and water are not available.

Warnings

For external use only. Flammable. Keep away from heat or flame

Do not use

- on children less than 2 months of age.
- on open skin wounds

When using this product

keep out of eyes, ears, and mouth. In case of contact with eyes, rinse eyes thoroughly with water.

Stop use and ask a doctor if

irritation or rash occurs. These may be signs of a serious condition.

Keep out of reach of children.

If swallowed, get medical help or contact Poison Control Center right away.

Directions

- Place enough product on hands to cover all surfaces. Rub hands together until dry.
- Supervise children under 6 years of age when using this product to avoid swallowing.

Other information

- Store between 15-30°C (59-86°F)
- Avoid freezing and excessive heat above 40°C (104°F)

Inactive ingredients:

Water(Aqua), Glycerin, Butylene Glycol, Aloe Barbadensis Leaf Juice, Carbomer, Aminomethyl Propanol, Isopropyl Myristate, Phenoxyethanol, Ethylhexylglycerin, Fragrance- Lavender.

Questions?

866-961-6181